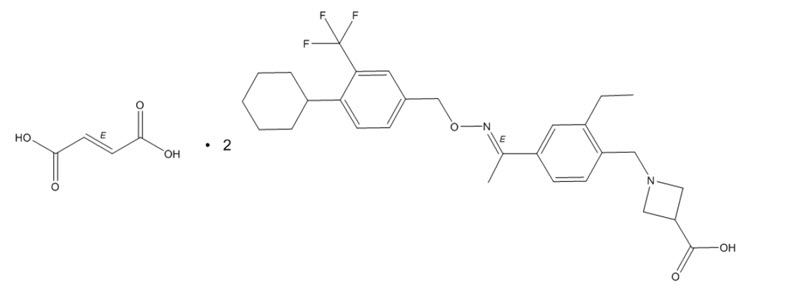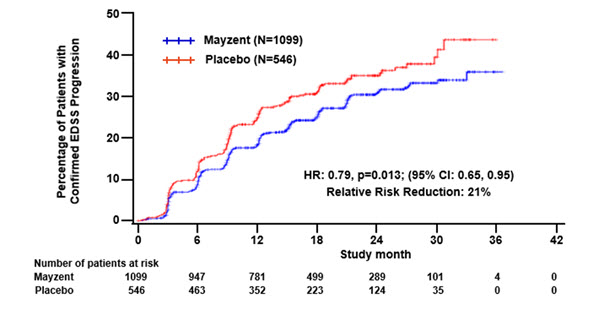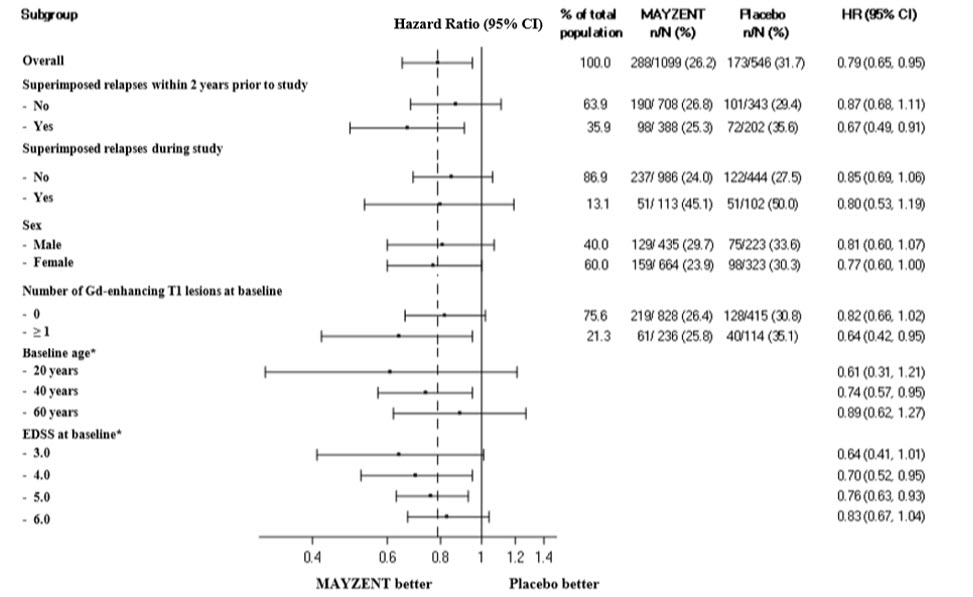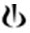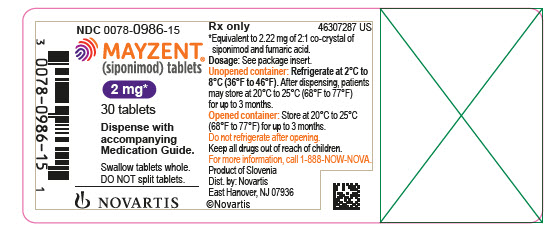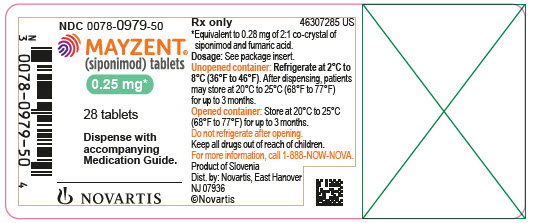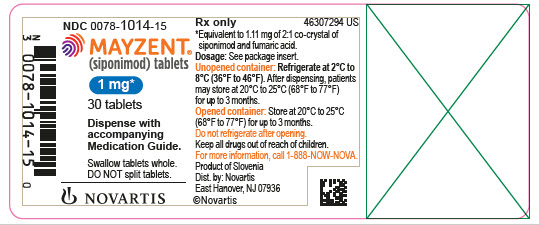 DRUG LABEL: MAYZENT
NDC: 0078-0979 | Form: TABLET, FILM COATED
Manufacturer: Novartis Pharmaceuticals Corporation
Category: prescription | Type: HUMAN PRESCRIPTION DRUG LABEL
Date: 20250821

ACTIVE INGREDIENTS: SIPONIMOD 0.25 mg/1 1
INACTIVE INGREDIENTS: LACTOSE MONOHYDRATE; CELLULOSE, MICROCRYSTALLINE; CROSPOVIDONE; GLYCERYL DIBEHENATE; SILICON DIOXIDE; POLYVINYL ALCOHOL, UNSPECIFIED; LECITHIN, SOYBEAN; XANTHAN GUM; TALC; TITANIUM DIOXIDE; FERRIC OXIDE RED; FERROSOFERRIC OXIDE

HIGHLIGHTS OF PRESCRIBING INFORMATION

These highlights do not include all the information needed to use MAYZENT safely and effectively. See full prescribing information for MAYZENT.
MAYZENT® (siponimod) tablets, for oral use
Initial U.S. Approval: 2019

1 INDICATIONS AND USAGE

MAYZENT is a sphingosine 1-phosphate (S1P) receptor modulator indicated for the treatment of relapsing forms of multiple sclerosis (MS), to include clinically isolated syndrome, relapsing-remitting disease, and active secondary progressive disease, in adults.

2 DOSAGE AND ADMINISTRATION

- Assessments are required prior to initiating MAYZENT. (2.1)
- Titration is required for treatment initiation. (2.2, 2.3)
- The recommended maintenance dosage is 2 mg. (2.2)
- The recommended maintenance dosage in patients with a CYP2C9*1/*3 or *2/*3 genotype is 1 mg. (2.3)
- Administer tablets whole; do not split, crush, or chew. (2.2, 2.3)
- First-dose monitoring is recommended for patients with sinus bradycardia, first- or second-degree [Mobitz type I] atrioventricular (AV) block, or a history of myocardial infarction or heart failure. (2.4)

3 DOSAGE FORMS AND STRENGTHS

Tablets: 0.25 mg, 1 mg, and 2 mg

4 CONTRAINDICATIONS

- Patients with a CYP2C9*3/*3 genotype. (4)
- In the last 6 months, experienced myocardial infarction, unstable angina, stroke, TIA, decompensated heart failure requiring hospitalization, or Class III/IV heart failure. (4)
- Presence of Mobitz type II second-degree, third-degree AV block, or sick sinus syndrome, unless patient has a functioning pacemaker. (4)

5 WARNINGS AND PRECAUTIONS

- Infections: MAYZENT may increase the risk. Obtain a complete blood count (CBC) before initiating treatment. Monitor for infection during treatment. Do not start in patients with active infection. (5.1)
- Progressive Multifocal Leukoencephalopathy (PML): Withhold MAYZENT at the first sign or symptom of PML. (5.2)
- Macular Edema: Increases the risk of macular edema. Obtain a baseline evaluation of the fundus, including the macula, near the start of treatment with MAYZENT. Conduct an evaluation of the fundus, including the macula, periodically while on therapy and any time there is a change in vision. Consider discontinuing MAYZENT if macular edema develops. Diabetes mellitus and uveitis increase the risk. (5.3)
- Bradyarrhythmia and Atrioventricular Conduction Delays: MAYZENT may result in a transient decrease in heart rate; titration is required for treatment initiation. Consider resting heart rate with concomitant beta-blocker use; obtain cardiologist consultation before concomitant use with other drugs that decrease heart rate. (5.4, 7.2, 7.3)
- Respiratory Effects: May cause a decline in pulmonary function. Assess pulmonary function (e.g., spirometry) if clinically indicated. (5.5)
- Liver Injury: Obtain liver enzyme results before initiation. Closely monitor patients with severe hepatic impairment. Discontinue if significant liver injury occurs. (5.6)
- Cutaneous Malignancies: Skin examination prior to or shortly after the start of treatment and periodically thereafter is recommended. Suspicious skin lesions should be evaluated. (5.7)
- Increased Blood Pressure: Monitor blood pressure during treatment. (5.8)
- Fetal Risk: Women of childbearing potential should use effective contraception during and for 10 days after stopping MAYZENT. (5.9)

6 ADVERSE REACTIONS

Most common adverse reactions (incidence greater than 10%) are headache, hypertension, and transaminase increases. (6.1)

To report SUSPECTED ADVERSE REACTIONS, contact Novartis Pharmaceuticals Corporation at 1-888-669-6682 or FDA at 1-800-FDA-1088 or www.fda.gov/medwatch.

7 DRUG INTERACTIONS

- Vaccination: Avoid live-attenuated vaccines during and for up to 4 weeks after treatment with MAYZENT. (7.4)
- CYP2C9 and Dual CYP2C9/3A4 Inhibitors: Strong CYP2C9 inhibitors increase siponimod exposure; concomitant use with MAYZENT is not recommended. Monitor for adverse reactions during concomitant use of MAYZENT with moderate CYP2C9 inhibitors or moderate CYP2C9/CYP3A4 dual inhibitors. (7.5)
- CYP2C9 and CYP3A4 Inducers: Dual moderate CYP2C9/strong CYP3A4 inducers decrease siponimod exposure; concomitant use with MAYZENT is not recommended. Monitor for loss of efficacy with concomitant use of MAYZENT and moderate or strong CYP3A4 inducers in patients with CYP2C9*1/*3 or *2/*3 genotypes. (7.6)

FULL PRESCRIBING INFORMATION

1 INDICATIONS AND USAGE

MAYZENT is indicated for the treatment of relapsing forms of multiple sclerosis (MS), to include clinically isolated syndrome, relapsing-remitting disease, and active secondary progressive disease, in adults.

2 DOSAGE AND ADMINISTRATION

2.1 Assessments Prior to First Dose of MAYZENT

Before initiation of treatment with MAYZENT, assess the following:

CYP2C9 Genotype Determination

Test patients for CYP2C9 variants to determine CYP2C9 genotype [see Dosage and Administration (2.2, 2.3), Contraindications (4) and Use in Specific Populations (8.6)]. An FDA-cleared or -approved test for the detection of CYP2C9 variants to direct the use of siponimod is not currently available.

Cardiac Evaluation

Obtain an electrocardiogram (ECG) to determine whether preexisting conduction abnormalities are present. In patients with certain preexisting conditions, advice from a cardiologist and first-dose monitoring is recommended [see Dosage and Administration (2.4) and Warnings and Precautions (5.4)].

Determine whether patients are taking drugs that could slow heart rate or atrioventricular (AV) conduction [see Drug Interactions (7.2, 7.3)].

Complete Blood Count

Review results of a recent complete blood count (CBC) [see Warnings and Precautions (5.1)].

Liver Function Tests

Obtain recent (i.e., within last 6 months) transaminase and bilirubin levels [see Warnings and Precautions (5.6)].

Ophthalmic Evaluation

Obtain a baseline evaluation of the fundus, including the macula, near the start of the treatment with MAYZENT [see Warnings and Precautions (5.3)].

Skin Examination

Obtain a baseline skin examination prior to or shortly after initiation of MAYZENT. If a suspicious skin lesion is observed, it should be promptly evaluated [see Warnings and Precautions (5.7)].

Current or Prior Medications

If patients are taking anti-neoplastic, immunosuppressive, or immune-modulating therapies, or if there is a history of prior use of these drugs, consider possible unintended additive immunosuppressive effects before initiating treatment with MAYZENT [see Warnings and Precautions (5.1) and Drug Interactions (7.1)].

Vaccinations

Test patients for antibodies to varicella zoster virus (VZV) before initiating MAYZENT; VZV vaccination of antibody-negative patients is recommended prior to commencing treatment with MAYZENT [see Warnings and Precautions (5.1)].

2.2 Recommended Dosage in Patients With CYP2C9 Genotypes *1/*1, *1/*2, or *2/*2

Maintenance Dosage

After treatment titration (see Treatment Initiation), the recommended maintenance dosage of MAYZENT is 2 mg taken orally once daily starting on Day 6. Dosage adjustment is required in patients with a CYP2C9*1/*3 or *2/*3 genotype [see Dosage and Administration (2.3)].

Administer tablets whole; do not split, crush, or chew MAYZENT tablets.

Treatment Initiation

Initiate MAYZENT with a 5-day titration, as shown in Table 1 [see Warnings and Precautions (5.4)]. A 12-tablet starter pack should be used for patients who will be titrated to the 2-mg maintenance dosage [see How Supplied/Storage and Handling (16.1, 16.2)].

Table 1 Dose Titration Regimen to Reach MAYZENT 2 mg Maintenance Dosage
Titration | Titration dose | Titration regimen
Day 1 | 0.25 mg | 1 x 0.25 mg
Day 2 | 0.25 mg | 1 x 0.25 mg
Day 3 | 0.50 mg | 2 x 0.25 mg
Day 4 | 0.75 mg | 3 x 0.25 mg
Day 5 | 1.25 mg | 5 x 0.25 mg

If one titration dose is missed for more than 24 hours, treatment needs to be reinitiated with Day 1 of the titration regimen.

2.3 Recommended Dosage in Patients With CYP2C9 Genotypes *1/*3 or *2/*3

Maintenance Dosage

In patients with a CYP2C9*1/*3 or *2/*3 genotype, after treatment titration (see Treatment Initiation), the recommended maintenance dosage of MAYZENT is 1 mg taken orally once daily starting on Day 5.

Administer tablets whole; do not split, crush, or chew MAYZENT tablets.

Treatment Initiation

Initiate MAYZENT with a 4-day titration, as shown in Table 2 [see Warnings and Precautions (5.4) and Use in Specific Populations (8.6)]. A 7-tablet starter pack should be used for patients who will be titrated to the 1-mg maintenance dosage [see How Supplied/Storage and Handling (16.1, 16.2)].

Table 2 Dose Titration Regimen to Reach MAYZENT 1 mg Maintenance Dosage
Titration | Titration dose | Titration regimen
Day 1 | 0.25 mg | 1 x 0.25 mg
Day 2 | 0.25 mg | 1 x 0.25 mg
Day 3 | 0.50 mg | 2 x 0.25 mg
Day 4 | 0.75 mg | 3 x 0.25 mg

If one titration dose is missed for more than 24 hours, treatment needs to be reinitiated with Day 1 of the titration regimen.

2.4 First Dose Monitoring in Patients With Certain Preexisting Cardiac Conditions

Because initiation of MAYZENT treatment results in a decrease in heart rate (HR), first-dose 6-hour monitoring is recommended for patients with sinus bradycardia [HR less than 55 beats per minute (bpm)], first- or second-degree [Mobitz type I] AV block, or a history of myocardial infarction or heart failure [see Contraindications (4), Warnings and Precautions (5.4), and Clinical Pharmacology (12.2)].

First Dose 6-Hour Monitoring

Administer the first dose of MAYZENT in a setting where resources to appropriately manage symptomatic bradycardia are available. Monitor patients for 6 hours after the first dose for signs and symptoms of bradycardia with hourly pulse and blood pressure measurement. Obtain an ECG in these patients at the end of the Day 1 observation period.

Additional Monitoring After 6-Hour Monitoring

If any of the following abnormalities are present after 6 hours (even in the absence of symptoms), continue monitoring until the abnormality resolves:

- The heart rate 6 hours postdose is less than 45 bpm
- The heart rate 6 hours postdose is at the lowest value postdose, suggesting that the maximum pharmacodynamic effect on the heart may not have occurred
- The ECG 6 hours postdose shows new onset second-degree or higher AV block

If post-dose symptomatic bradycardia, bradyarrhythmia, or conduction-related symptoms occur, or if ECG 6 hours post-dose shows new onset second-degree or higher AV block or QTc greater than or equal to 500 msec, initiate appropriate management, begin continuous ECG monitoring, and continue monitoring until the symptoms have resolved if no pharmacological treatment is required. If pharmacological treatment is required, continue monitoring overnight and repeat 6-hour monitoring after the second dose.

Advice from a cardiologist should be sought to determine the most appropriate monitoring strategy (which may include overnight monitoring) during treatment initiation, if treatment with MAYZENT is considered in patients:

- With some preexisting heart and cerebrovascular conditions [see Warnings and Precautions (5.4)]
- With a prolonged QTc interval before dosing or during the 6-hour observation, or at additional risk for QT prolongation, or on concurrent therapy with QT prolonging drugs with a known risk of torsades de pointes [see Warnings and Precautions (5.4) and Drug Interactions (7.2)]
- Receiving concurrent therapy with drugs that slow heart rate or AV conduction [see Drug Interactions (7.2, 7.3)]

2.5 Reinitiation of MAYZENT After Treatment Interruption

After the initial titration is complete, if MAYZENT treatment is interrupted for 4 or more consecutive daily doses, reinitiate treatment with Day 1 of the titration regimen [see Dosage and Administration (2.2, 2.3)]; also complete first-dose monitoring in patients for whom it is recommended [see Dosage and Administration (2.4)].

3 DOSAGE FORMS AND STRENGTHS

0.25 mg tablet: Pale red, unscored, round biconvex film-coated tablet with beveled edges, debossed with on one side and ‘T’ on other side.

1 mg tablet: Violet white, unscored, round biconvex film-coated tablet with beveled edges, debossed with on one side and ‘L’ on other side.

2 mg tablet: Pale yellow, unscored, round biconvex film-coated tablet with beveled edges, debossed with on one side and ‘II’ on other side.

4 CONTRAINDICATIONS

MAYZENT is contraindicated in patients who have:

- A CYP2C9*3/*3 genotype [see Use in Specific Populations (8.6) and Clinical Pharmacology (12.5)]
- In the last 6 months experienced myocardial infarction, unstable angina, stroke, TIA, decompensated heart failure requiring hospitalization, or Class III or IV heart failure
- Presence of Mobitz type II second-degree, third-degree AV block, or sick sinus syndrome, unless patient has a functioning pacemaker [see Warnings and Precautions (5.4)]

5 WARNINGS AND PRECAUTIONS

5.1 Infections

Risk of Infections

MAYZENT causes a dose-dependent reduction in peripheral lymphocyte count to 20% to 30% of baseline values because of reversible sequestration of lymphocytes in lymphoid tissues. MAYZENT may therefore increase the risk of infections, some serious in nature [see Clinical Pharmacology (12.2)]. Life-threatening and rare fatal infections have occurred in association with MAYZENT.

In Study 1 [see Clinical Studies (14)], the overall rate of infections was comparable between the MAYZENT-treated patients and those on placebo (49.0% vs. 49.1%, respectively). However, herpes zoster, herpes infection, bronchitis, sinusitis, upper respiratory infection, and fungal skin infection were more common in MAYZENT-treated patients. In Study 1, serious infections occurred at a rate of 2.9% in MAYZENT-treated patients compared to 2.5% of patients receiving placebo.

Before initiating treatment with MAYZENT, results from a recent CBC (i.e., within 6 months or after discontinuation of prior therapy) should be reviewed.

Initiation of treatment with MAYZENT should be delayed in patients with severe active infection until resolution. Because residual pharmacodynamic effects, such as lowering effects on peripheral lymphocyte count, may persist for up to 3 to 4 weeks after discontinuation of MAYZENT, vigilance for infection should be continued throughout this period [see Warnings and Precautions (5.13)].

Effective diagnostic and therapeutic strategies should be employed in patients with symptoms of infection while on therapy. Suspension of treatment with MAYZENT should be considered if a patient develops a serious infection.

Cryptococcal Infections

Cases of fatal cryptococcal meningitis (CM) and disseminated cryptococcal infections have been reported with another sphingosine 1-phosphate (S1P) receptor modulator. Rare cases of CM have also occurred with MAYZENT. Physicians should be vigilant for clinical symptoms or signs of CM. Patients with symptoms or signs consistent with a cryptococcal infection should undergo prompt diagnostic evaluation and treatment. MAYZENT treatment should be suspended until a cryptococcal infection has been excluded. If CM is diagnosed, appropriate treatment should be initiated.

Herpes Viral Infections

Cases of herpes viral infection, including cases of meningitis or meningoencephalitis caused by VZV reactivation, have been reported with MAYZENT. In Study 1, the rate of herpetic infections was 4.6% in MAYZENT-treated patients compared to 3.0% of patients receiving placebo. In Study 1, an increase in the rate of herpes zoster infections was reported in 2.5% of MAYZENT-treated patients compared to 0.7% of patients receiving placebo. Patients without a healthcare professional-confirmed history of varicella (chickenpox) or without documentation of a full course of vaccination against VZV should be tested for antibodies to VZV before initiating MAYZENT (see Vaccinations below).

Prior and Concomitant Treatment with Anti-neoplastic, Immune-Modulating, or Immunosuppressive Therapies

Anti-neoplastic, immune-modulating, or immunosuppressive therapies (including corticosteroids) should be coadministered with caution because of the risk of additive immune system effects during such therapy [see Drug Interactions (7.1)].

Vaccinations

Patients without a healthcare professional-confirmed history of chickenpox or without documentation of a full course of vaccination against VZV should be tested for antibodies to VZV before initiating MAYZENT treatment. A full course of vaccination for antibody-negative patients with varicella vaccine is recommended prior to commencing treatment with MAYZENT, following which initiation of treatment with MAYZENT should be postponed for 4 weeks to allow the full effect of vaccination to occur.

Vaccinations may be less effective if administered during MAYZENT treatment.

The use of live-attenuated vaccines should be avoided while patients are taking MAYZENT and for 4 weeks after stopping treatment [see Drug Interactions (7.4)].

5.2 Progressive Multifocal Leukoencephalopathy

Cases of progressive multifocal leukoencephalopathy (PML) have occurred in patients with MS treated with S1P receptor modulators, including MAYZENT. PML is an opportunistic viral infection of the brain caused by the JC virus (JCV) that typically only occurs in patients who are immunocompromised, and that usually leads to death or severe disability. PML has occurred in MAYZENT-treated patients who had not been treated previously with natalizumab (which has a known association with PML), were not taking any other immunosuppressive or immunomodulatory medications concomitantly, and did not have any ongoing systemic medical conditions resulting in compromised immune system function. Longer treatment duration increases the risk of PML in patients treated with S1P receptor modulators: the majority of cases of PML associated with S1P receptor modulators, including MAYZENT, have occurred in patients treated for at least 18 months.

At the first sign or symptom suggestive of PML, withhold MAYZENT and perform an appropriate diagnostic evaluation. Typical symptoms associated with PML are diverse, progress over days to weeks and include progressive weakness on one side of the body or clumsiness of limbs, disturbance of vision, and changes in thinking, memory, and orientation leading to confusion and personality changes. MRI findings may be apparent before clinical signs or symptoms. Cases of PML, diagnosed based on MRI findings and the detection of JCV DNA in the cerebrospinal fluid in the absence of clinical signs or symptoms specific to PML, have been reported in patients treated with MS medications associated with PML, including S1P receptor modulators. Many of these patients subsequently became symptomatic with PML. Therefore, monitoring with MRI for signs that may be consistent with PML may be useful, and any suspicious findings should lead to further investigation to allow for an early diagnosis of PML, if present. Lower PML-related mortality and morbidity have been reported following discontinuation of another MS medication associated with PML in patients with PML who were initially asymptomatic compared to patients with PML who had characteristic clinical signs and symptoms at diagnosis. It is not known whether these differences are due to early detection and discontinuation of MS treatment or due to differences in disease in these patients.

If PML is confirmed, treatment with MAYZENT should be discontinued.

Immune reconstitution inflammatory syndrome (IRIS) has been reported in patients treated with S1P receptor modulators, including MAYZENT, who developed PML and subsequently discontinued treatment. IRIS presents as a clinical decline in the patient’s condition that may be rapid, can lead to serious neurological complications or death, and is often associated with characteristic changes on MRI. The time to onset of IRIS in patients with PML was generally within a few months after S1P receptor modulator discontinuation. Monitoring for development of IRIS and appropriate treatment of the associated inflammation should be undertaken.

5.3 Macular Edema

S1P receptor modulators, including MAYZENT, have been associated with an increased risk of macular edema. Obtain a baseline evaluation of the fundus, including the macula, near the start of treatment with MAYZENT. Perform an examination of the fundus, including the macula, periodically while on therapy, and any time there is a change in vision.

Macular edema was reported in 1.8% of MAYZENT-treated patients compared to 0.2% of patients receiving placebo. The majority of cases occurred within the first four months of therapy.

Continuation of MAYZENT therapy in patients with macular edema has not been evaluated. Macular edema over an extended period of time (i.e., 6 months) can lead to permanent visual loss. Consider discontinuing MAYZENT if macular edema develops; this decision should include an assessment of the potential benefits and risks for the individual patient. The risk of recurrence after rechallenge has not been evaluated.

Macular Edema in Patients with a History of Uveitis or Diabetes Mellitus

Patients with a history of uveitis and patients with diabetes mellitus are at increased risk of macular edema during MAYZENT therapy. In the clinical trial experience in adult patients with all doses of MAYZENT, the rate of macular edema was higher in MS patients with a history of uveitis or diabetes mellitus compared to those without a history of these diseases (approximately 10% vs. 2%, respectively).

5.4 Bradyarrhythmia and Atrioventricular Conduction Delays

Since initiation of MAYZENT treatment results in a transient decrease in heart rate and atrioventricular conduction delays, an up-titration scheme should be used to reach the maintenance dosage of MAYZENT [see Dosage and Administration (2.2, 2.3) and Clinical Pharmacology (12.2)].

MAYZENT was not studied in patients who had:

- In the last 6 months experienced myocardial infarction, unstable angina, stroke, transient ischemic attack (TIA), or decompensated heart failure requiring hospitalization
- New York Heart Association Class II-IV heart failure
- Cardiac conduction or rhythm disorders, including complete left bundle branch block, sinus arrest or sino-atrial block, symptomatic bradycardia, sick sinus syndrome, Mobitz type II second degree AV-block or higher-grade AV-block (either history or observed at screening), unless patient has a functioning pacemaker
- Significant QT prolongation (QTc greater than 500 msec)
- Arrhythmias requiring treatment with Class Ia or Class III anti-arrhythmic drugs [see Drug Interactions (7.2)]

Reduction in Heart Rate

After the first titration dose of MAYZENT, the heart rate decrease starts within an hour, and the Day 1 decline is maximal at approximately 3 to 4 hours. With continued up-titration, further heart rate decreases are seen on subsequent days, with maximal decrease from Day 1-baseline reached on Day 5 to Day 6. The highest daily post-dose decrease in absolute hourly mean heart rate is observed on Day 1, with the pulse declining on average 5 to 6 bpm. Post-dose declines on the following days are less pronounced. With continued dosing, heart rate starts increasing after Day 6 and reaches placebo levels within 10 days after treatment initiation.

In Study 1, bradycardia occurred in 4.4% of MAYZENT-treated patients compared to 2.9% of patients receiving placebo. Patients who experienced bradycardia were generally asymptomatic. Few patients experienced symptoms, including dizziness or fatigue, and these symptoms resolved within 24 hours without intervention [see Adverse Reactions (6.1)]. Heart rates below 40 bpm were rarely observed.

Atrioventricular Conduction Delays

Initiation of MAYZENT treatment has been associated with transient atrioventricular conduction delays that follow a similar temporal pattern as the observed decrease in heart rate during dose titration. The AV conduction delays manifested in most of the cases as first-degree AV block (prolonged PR interval on ECG), which occurred in 5.1% of MAYZENT-treated patients and in 1.9% of patients receiving placebo in Study 1. Second-degree AV blocks, usually Mobitz type I (Wenckebach), have been observed at the time of treatment initiation with MAYZENT in less than 1.7% of patients in clinical trials. The conduction abnormalities typically were transient, asymptomatic, resolved within 24 hours, rarely required treatment with atropine, and did not require discontinuation of MAYZENT treatment.

If treatment with MAYZENT is considered, advice from a cardiologist should be sought in patients with:

- Significant QT prolongation (QTc greater than 500 msec)
- Arrhythmias requiring treatment with Class Ia or Class III anti-arrhythmic drugs [see Drug Interactions (7.2)]
- Ischemic heart disease, heart failure, history of cardiac arrest or myocardial infarction, cerebrovascular disease, and uncontrolled hypertension
- A history of second-degree Mobitz type II or higher AV block, sick-sinus syndrome, or sino-atrial heart block [see Contraindications (4)]

Treatment-Initiation Recommendations

- Obtain an ECG in all patients to determine whether preexisting conduction abnormalities are present.
- In all patients, a dose titration is recommended for initiation of MAYZENT treatment to help reduce cardiac effects [see Dosage and Administration (2.2, 2.3)].
- In patients with sinus bradycardia (HR less than 55 bpm), first- or second-degree [Mobitz type I] AV block, or a history of myocardial infarction or heart failure, if not contraindicated, ECG testing and first-dose monitoring is recommended [see Dosage and Administration (2.1, 2.4) and Contraindications (4)].
- Since significant bradycardia may be poorly tolerated in patients with history of cardiac arrest, cerebrovascular disease, uncontrolled hypertension, or severe untreated sleep apnea, MAYZENT is not recommended in these patients. If treatment is considered, advice from a cardiologist should be sought prior to initiation of treatment in order to determine the most appropriate monitoring strategy.
- Use of MAYZENT in patients with a history of recurrent syncope or symptomatic bradycardia should be based on an overall benefit-risk assessment. If treatment is considered, advice from a cardiologist should be sought prior to initiation of treatment in order to determine the most appropriate monitoring.
- Experience with MAYZENT is limited in patients receiving concurrent therapy with drugs that decrease heart rate (e.g., beta-blockers, calcium channel blockers - diltiazem and verapamil, and other drugs that may decrease heart rate, such as ivabradine and digoxin). Concomitant use of these drugs during MAYZENT initiation may be associated with severe bradycardia and heart block.
  - For patients receiving a stable dose of a beta-blocker, the resting heart rate should be considered before introducing MAYZENT treatment. If the resting heart rate is greater than 50 bpm under chronic beta-blocker treatment, MAYZENT can be introduced. If resting heart rate is less than or equal to 50 bpm, beta-blocker treatment should be interrupted until the baseline heart rate is greater than 50 bpm. Treatment with MAYZENT can then be initiated and treatment with a beta-blocker can be reinitiated after MAYZENT has been up-titrated to the target maintenance dosage [see Drug Interactions (7.3)].
  - For patients taking other drugs that decrease heart rate, treatment with MAYZENT should generally not be initiated without consultation from a cardiologist because of the potential additive effect on heart rate [see Dosage and Administration (2.4) and Drug Interactions (7.2)].

Missed Dose During Treatment Initiation and Reinitiation of Therapy Following Interruption

If a titration dose is missed, or if 4 or more consecutive daily doses are missed during maintenance treatment, reinitiate Day 1 of the dose titration and follow titration monitoring recommendations [see Dosage and Administration (2.2, 2.3)].

5.5 Respiratory Effects

Dose-dependent reductions in absolute forced expiratory volume over 1 second (FEV1) were observed in MAYZENT-treated patients as early as 3 months after treatment initiation. In a placebo-controlled trial in adult patients, the decline in absolute FEV1 from baseline compared to placebo was 88 mL [95% confidence interval (CI): 139, 37] at 2 years. The mean difference between MAYZENT-treated patients and patients receiving placebo in percent predicted FEV1 at 2 years was 2.8% (95% CI: -4.5, -1.0). There is insufficient information to determine the reversibility of the decrease in FEV1 after drug discontinuation. In Study 1, five patients discontinued MAYZENT because of decreases in pulmonary function testing. MAYZENT has been tested in MS patients with mild to moderate asthma and chronic obstructive pulmonary disease. The changes in FEV1 were similar in this subgroup compared with the overall population. Spirometric evaluation of respiratory function should be performed during therapy with MAYZENT if clinically indicated.

5.6 Liver Injury

Elevations of transaminases may occur in MAYZENT-treated patients. Recent (i.e., within last 6 months) transaminase and bilirubin levels should be reviewed before initiation of MAYZENT therapy.

In Study 1, elevations in transaminases and bilirubin were observed in 10.1% of MAYZENT-treated patients compared to 3.7% of patients receiving placebo, mainly because of transaminase [alanine aminotransferase/aspartate aminotransferase/gamma-glutamyltransferase (ALT/AST/GGT)] elevations.

In Study 1, ALT or AST increased to three and five times the upper limit of normal (ULN) in 5.6% and 1.4% of MAYZENT-treated patients, respectively, compared to 1.5% and 0.5% of patients receiving placebo, respectively. ALT or AST increased eight and ten times ULN in MAYZENT-treated patients (0.5% and 0.2%, respectively) compared to no patients receiving placebo. The majority of elevations occurred within 6 months of starting treatment. ALT levels returned to normal within approximately 1 month after discontinuation of MAYZENT. In clinical trials, MAYZENT was discontinued if the elevation exceeded a 3-fold increase and the patient showed symptoms related to hepatic dysfunction.

Patients who develop symptoms suggestive of hepatic dysfunction, such as unexplained nausea, vomiting, abdominal pain, fatigue, anorexia, rash with eosinophilia, or jaundice and/or dark urine during treatment, should have liver enzymes checked. MAYZENT should be discontinued if significant liver injury is confirmed.

Although there are no data to establish that patients with preexisting liver disease are at increased risk to develop elevated liver function test values when taking MAYZENT, caution should be exercised when using MAYZENT in patients with a history of significant liver disease.

5.7 Cutaneous Malignancies

The risk of cutaneous malignancies (including basal cell carcinoma (BCC), squamous cell carcinoma (SCC), and melanoma) is increased in patients treated with S1P receptor modulators. Use of MAYZENT has been associated with an increased risk of BCC and SCC. In Study 1, the incidence of BCC and SCC was 1.1% and 0.2%, respectively, in MAYZENT-treated patients [see Adverse Reactions (6.1)]. Cases of other cutaneous malignancies, including melanoma, have also been reported in patients treated with MAYZENT and in patients treated with other S1P receptor modulators. Kaposi’s sarcoma and Merkel cell carcinoma have also been reported in patients treated with S1P receptor modulators in the postmarketing setting.

Skin examinations are recommended prior to or shortly after the start of treatment and periodically thereafter for all patients, particularly those with risk factors for skin cancer. Providers and patients are advised to monitor for suspicious skin lesions. If a suspicious skin lesion is observed, it should be promptly evaluated. As usual for patients with increased risk for skin cancer, exposure to sunlight and ultraviolet (UV) light should be limited by wearing protective clothing and using a sunscreen with a high protection factor. Concomitant phototherapy with UV-B radiation or PUVA photochemotherapy is not recommended in patients taking MAYZENT.

5.8 Increased Blood Pressure

In Study 1, MAYZENT-treated patients had an average increase over placebo of approximately 3 mmHg in systolic pressure and 1.2 mmHg in diastolic pressure, which was first detected after approximately 1 month of treatment initiation and persisted with continued treatment. Hypertension was reported as an adverse reaction in 12.5% of MAYZENT-treated patients and in 9.2% of patients receiving placebo. Blood pressure should be monitored during treatment with MAYZENT and managed appropriately.

5.9 Fetal Risk

Based on animal studies, MAYZENT may cause fetal harm [see Use in Specific Populations (8.1)]. Because it takes approximately 10 days to eliminate MAYZENT from the body, women of childbearing potential should use effective contraception to avoid pregnancy during and for 10 days after stopping MAYZENT treatment.

5.10 Posterior Reversible Encephalopathy Syndrome

Rare cases of posterior reversible encephalopathy syndrome (PRES) have been reported in patients receiving an S1P receptor modulator. Such events have not been reported for MAYZENT-treated patients in the development program. However, should a MAYZENT-treated patient develop any unexpected neurological or psychiatric symptoms/signs (e.g., cognitive deficits, behavioral changes, cortical visual disturbances, or any other neurological cortical symptoms/signs), any symptom/sign suggestive of an increase of intracranial pressure, or accelerated neurological deterioration, the physician should promptly schedule a complete physical and neurological examination and should consider an MRI. Symptoms of PRES are usually reversible but may evolve into ischemic stroke or cerebral hemorrhage. Delay in diagnosis and treatment may lead to permanent neurological sequelae. If PRES is suspected, MAYZENT should be discontinued.

5.11 Unintended Additive Immunosuppressive Effects From Prior Treatment With Immunosuppressive or Immune-Modulating Therapies

When switching from drugs with prolonged immune effects, the half-life and mode of action of these drugs must be considered to avoid unintended additive immunosuppressive effects while at the same time minimizing risk of disease reactivation, when initiating MAYZENT.

Initiating treatment with MAYZENT after treatment with alemtuzumab is not recommended [see Drug Interactions (7.1)].

5.12 Severe Increase in Disability After Stopping MAYZENT

Severe exacerbation of disease, including disease rebound, has been rarely reported after discontinuation of an S1P receptor modulator. The possibility of severe exacerbation of disease should be considered after stopping MAYZENT treatment. Patients should be observed for a severe increase in disability upon MAYZENT discontinuation and appropriate treatment should be instituted, as required.

After stopping MAYZENT in the setting of PML, monitor for development of immune reconstitution inflammatory syndrome (PML-IRIS) [see Warnings and Precautions (5.2)].

5.13 Immune System Effects After Stopping MAYZENT

After stopping MAYZENT therapy, siponimod remains in the blood for up to 10 days. Starting other therapies during this interval will result in concomitant exposure to siponimod.

Lymphocyte counts returned to the normal range in 90% of patients within 10 days of stopping therapy [see Clinical Pharmacology (12.2)]. However, residual pharmacodynamics effects, such as lowering effects on peripheral lymphocyte count, may persist for up to 3 to 4 weeks after the last dose. Use of immunosuppressants within this period may lead to an additive effect on the immune system, and therefore caution should be applied 3 to 4 weeks after the last dose of MAYZENT [see Drug Interactions (7.1)].

6 ADVERSE REACTIONS

The following serious adverse reactions are described elsewhere in the labeling:

- Infections [see Warnings and Precautions (5.1)]
- Progressive Multifocal Leukoencephalopathy [see Warnings and Precautions (5.2)]
- Macular Edema [see Warnings and Precautions (5.3)]
- Bradyarrhythmia and Atrioventricular Conduction Delays [see Warnings and Precautions (5.4)]
- Respiratory Effects [see Warnings and Precautions (5.5)]
- Liver Injury [see Warnings and Precautions (5.6)]
- Cutaneous Malignancies [see Warnings and Precautions (5.7)]
- Increased Blood Pressure [see Warnings and Precautions (5.8)]
- Fetal Risk [see Warnings and Precautions (5.9)]
- Posterior Reversible Encephalopathy Syndrome [see Warnings and Precautions (5.10)]
- Unintended Additive Immunosuppressive Effects From Prior Treatment With Immunosuppressive or Immune-Modulating Therapies [see Warnings and Precautions (5.11)]
- Severe Increase in Disability After Stopping MAYZENT [see Warnings and Precautions (5.12)]
- Immune System Effects After Stopping MAYZENT [see Warnings and Precautions (5.13)]

6.1 Clinical Trials Experience

Because clinical trials are conducted under widely varying conditions, adverse reaction rates observed in the clinical trials of a drug cannot be directly compared to rates in the clinical trials of another drug and may not reflect the rates observed in practice.

A total of 1737 MS patients have received MAYZENT at doses of at least 2 mg daily. These patients were included in Study 1 [see Clinical Studies (14)] and in a Phase 2 placebo-controlled study in patients with MS. In Study 1, 67% of MAYZENT-treated patients completed the double-blind part of the study, compared to 59.0% of patients receiving placebo. Adverse events led to discontinuation of treatment in 8.5% of MAYZENT-treated patients, compared to 5.1% of patients receiving placebo. The most common adverse reactions (incidence at least 10%) in MAYZENT-treated patients in Study 1 were headache, hypertension, and transaminase increases.

Table 3 lists adverse reactions that occurred in at least 5% of MAYZENT-treated patients and at a rate at least 1% higher than in patients receiving placebo.

Table 3 Adverse Reactions Reported in Study 1 (Occurring in at Least 5% of MAYZENT-Treated Patients and at a Rate at Least 1% Higher Than in Patients Receiving Placebo)
Adverse reaction | MAYZENT 2 mg (N = 1099) % | Placebo (N = 546) %
Headachea | 15 | 14
Hypertensionb | 13 | 9
Transaminase increasedc | 11 | 3
Falls | 11 | 10
Edema peripherald | 8 | 4
Nausea | 7 | 4
Dizziness | 7 | 5
Diarrhea | 6 | 4
Bradycardiae | 6 | 3
Pain in extremityf | 6 | 4
Terms were combined as follows:
aheadache, tension headache, sinus headache, cervicogenic headache, drug withdrawal headache, and procedural headache.
bhypertension, blood pressure increased, blood pressure systolic increased, essential hypertension, blood pressure diastolic increased.
calanine aminotransferase increased, gamma-glutamyltransferase increased, hepatic enzyme increased, aspartate aminotransferase increased,
blood alkaline phosphatase increased, liver function test increased, hepatic function abnormal, liver function test abnormal, transaminases increased.
dedema peripheral, joint swelling, fluid retention, swelling face.
ebradycardia, sinus bradycardia, heart rate decreased.
fpain in extremity and limb discomfort.

The following adverse reactions have occurred in less than 5% of MAYZENT-treated patients but at a rate at least 1% higher than in patients receiving placebo: herpes zoster, lymphopenia, seizure, tremor, macular edema, AV block (1st and 2nd degree), asthenia, and pulmonary function test decreased [see Warnings and Precautions (5.1, 5.3, 5.4, 5.5)].

Seizures

In Study 1, cases of seizures were reported in 1.7% of MAYZENT-treated patients, compared to 0.4% in patients receiving placebo. It is not known whether these events were related to the effects of MS, to MAYZENT, or to a combination of both.

Respiratory Effects

Dose-dependent reductions in forced expiratory volume over 1 second (FEV1) were observed in patients treated with MAYZENT [see Warnings and Precautions (5.5)].

Vascular Events

Vascular events, including ischemic strokes, pulmonary embolisms, and myocardial infarctions, were reported in 3.0% of MAYZENT-treated patients compared to 2.6% of patients receiving placebo. Some of these events were fatal. Physicians and patients should remain alert for the development of vascular events throughout treatment, even in the absence of previous vascular symptoms. Patients should be informed about the symptoms of cardiac or cerebral ischemia caused by vascular events and the steps to take if they occur.

Malignancies

Malignancies, such as BCC, SCC, malignant melanoma, and seminoma were reported in MAYZENT-treated patients in Study 1 (in the core or extension parts). An increased risk of cutaneous malignancies has been reported in association with S1P receptor modulators. The risk of BCC and SCC is increased in MAYZENT-treated patients [see Warnings and Precautions (5.7)].

6.2 Postmarketing Experience

The following adverse reactions have been identified during postapproval use of MAYZENT. Because these reactions are reported voluntarily from a population of uncertain size, it is not always possible to reliably estimate their frequency or establish a causal relationship to drug exposure.

Infections and Infestations: Progressive multifocal leukoencephalopathy [see Warnings and Precautions (5.2)].

7 DRUG INTERACTIONS

7.1 Anti-Neoplastic, Immune-Modulating, or Immunosuppressive Therapies

MAYZENT has not been studied in combination with anti-neoplastic, immune-modulating, or immunosuppressive therapies. Caution should be used during concomitant administration because of the risk of additive immune effects during such therapy and in the weeks following administration [see Warnings and Precautions (5.1)].

When switching from drugs with prolonged immune effects, the half-life and mode of action of these drugs must be considered in order to avoid unintended additive immunosuppressive effects [see Warnings and Precautions (5.11)].

Because of the characteristics and duration of alemtuzumab immune suppressive effects, initiating treatment with MAYZENT after alemtuzumab is not recommended.

MAYZENT can generally be started immediately after discontinuation of beta interferon or glatiramer acetate.

7.2 Anti-Arrhythmic Drugs, QT Prolonging Drugs, Drugs That May Decrease Heart Rate

MAYZENT has not been studied in patients taking QT prolonging drugs.

Class Ia (e.g., quinidine, procainamide) and Class III (e.g., amiodarone, sotalol) antiarrhythmic drugs have been associated with cases of Torsades de Pointes in patients with bradycardia. If treatment with MAYZENT is considered, advice from a cardiologist should be sought.

Because of the potential additive effects on heart rate, treatment with MAYZENT should generally not be initiated in patients who are concurrently treated with QT prolonging drugs with known arrhythmogenic properties, heart-rate lowering calcium channel blockers (e.g., verapamil, diltiazem), or other drugs that may decrease heart rate (e.g., ivabradine, digoxin) [see Warnings and Precautions (5.4) and Drug Interactions (7.3)]. If treatment with MAYZENT is considered, advice from a cardiologist should be sought regarding the switch to non-heart-rate lowering drugs or appropriate monitoring for treatment initiation.

7.3 Beta-Blockers

Caution should be applied when MAYZENT is initiated in patients receiving treatment with a beta-blocker because of the additive effects on lowering heart rate; temporary interruption of the beta-blocker treatment may be needed prior to initiation of MAYZENT [see Warnings and Precautions (5.4)]. Beta-blocker treatment can be initiated in patients receiving stable doses of MAYZENT [see Clinical Pharmacology (12.2)].

7.4 Vaccination

During and for up to one month after discontinuation of treatment with MAYZENT, vaccinations may be less effective [see Warnings and Precautions (5.1)].

The use of live-attenuated vaccines may carry the risk of infection and should therefore be avoided during MAYZENT treatment and for up to 4 weeks after discontinuation of treatment with MAYZENT [see Warnings and Precautions (5.1)].

7.5 CYP2C9 and Dual CYP2C9/CYP3A4 Inhibitors

Concomitant use of MAYZENT and drugs that cause strong CYP2C9 inhibition is not recommended because a clinically relevant increase in exposure to siponimod is anticipated. Monitor for adverse reactions during concomitant use of MAYZENT with moderate CYP2C9 inhibitors or moderate CYP2C9/CYP3A4 dual inhibitors [see Clinical Pharmacology (12.3)].

7.6 CYP2C9 and CYP3A4 Inducers

Because of an expected significant reduction in siponimod exposure, concomitant use of MAYZENT and dual moderate CYP2C9/strong CYP3A4 inducers in patients with all CYP2C9 genotypes is not recommended.

Monitor for loss of efficacy with concomitant use of MAYZENT and moderate or strong CYP3A4 inducers in patients with CYP2C9*1/*3 or *2/*3 genotype [see Clinical Pharmacology (12.3)].

8 USE IN SPECIFIC POPULATIONS

8.1 Pregnancy

Pregnancy Exposure Registry

There is a pregnancy exposure registry that monitors pregnancy outcomes in women exposed to MAYZENT during pregnancy. Healthcare providers are encouraged to enroll pregnant patients, or pregnant women may register themselves in the MotherToBaby Pregnancy Study in Multiple Sclerosis by calling 1-877-311-8972, sending an email to MotherToBaby@health.ucsd.edu, or visiting www.mothertobaby.org/join-study.

Risk Summary

There are no adequate data on the developmental risk associated with the use of MAYZENT in pregnant women. Based on animal data and its mechanism of action, MAYZENT can cause fetal harm when administered to a pregnant woman (see Data). Reproductive and developmental studies in pregnant rats and rabbits have demonstrated MAYZENT-induced embryotoxicity and fetotoxicity in rats and rabbits and teratogenicity in rats. Increased incidences of post-implantation loss and fetal abnormalities (external, urogenital, and skeletal) in rat and of embryo-fetal deaths, abortions, and fetal variations (skeletal and visceral) in rabbit were observed following prenatal exposure to siponimod starting at a dose 2 times the exposure in humans at the highest recommended dose of 2 mg/day.

In the US general population, the estimated background risk of major birth defects and miscarriage in clinically recognized pregnancies is 2% to 4% and 15% to 20%, respectively. The background risk of major birth defects and miscarriage for the indicated population is unknown.

Data

Animal Data

When siponimod (0, 1, 5, or 40 mg/kg) was orally administered to pregnant rats during the period of organogenesis, post-implantation loss and fetal malformations (visceral and skeletal) were increased at the lowest dose tested, the only dose with fetuses available for evaluation. A no-effect dose for adverse effects on embryo-fetal development in rats was not identified. Plasma exposure AUC at the lowest dose tested was approximately 18 times that in humans at the recommended human dose (RHD) of 2 mg/day.

When siponimod (0, 0.1, 1, or 5 mg/kg) was orally administered to pregnant rabbits during the period of organogenesis, embryolethality and increased incidences of fetal skeletal variations were observed at all but the lowest dose tested. Plasma exposure (AUC) at the no-effect dose (0.1 mg/kg) for adverse effects on embryo-fetal development in rabbits is less than that in humans at the RHD.

When siponimod (0, 0.05, 0.15, or 0.5 mg/kg) was orally administered to female rats throughout pregnancy and lactation, increased mortality, decreased body weight, and delayed sexual maturation were observed in the offspring at all but the lowest dose tested. An increase in malformations was observed at all doses. A no-effect dose for adverse effects on pre- and postnatal development in rats was not identified. The lowest dose tested (0.05 mg/kg) is less than the RHD, on a mg/m^2 basis.

8.2 Lactation

Risk Summary

There are no data on the presence of siponimod in human milk, the effects of MAYZENT on the breastfed infant, or the effects of the drug on milk production. A study in lactating rats has shown excretion of siponimod and/or its metabolites in milk. The developmental and health benefits of breastfeeding should be considered along with the mother’s clinical need for MAYZENT and any potential adverse effects on the breastfed infant from MAYZENT or from the underlying maternal condition.

8.3 Females and Males of Reproductive Potential

Contraception

Females

Before initiation of MAYZENT treatment, women of childbearing potential should be counseled on the potential for a serious risk to the fetus and the need for effective contraception during treatment with MAYZENT [see Use in Specific Populations (8.1)]. Since it takes approximately 10 days to eliminate the compound from the body after stopping treatment, the potential risk to the fetus may persist and women should use effective contraception during this period [see Warnings and Precautions (5.9)].

8.4 Pediatric Use

Safety and effectiveness in pediatric patients have not been established.

Juvenile Animal Toxicity Data

Oral administration of siponimod (0, 5, 15, or 50 mg/kg/day) to young rats from postnatal Day 25 to Day 70 resulted in mortality, lung histopathology (alveolar/interstitial edema, fibrin, interstitial mixed cell infiltration) and decrease in body weight gain at the mid and high doses. Neurobehavioral impairment (decreased acoustic startle response) was observed at the high dose but was reversible by the end of the recovery period. Decrease in immune function (T-cell dependent antibody response) was observed at all doses and had not fully recovered by 4 weeks after the end of dosing. A no-effect dose for adverse effects in juvenile animals was not identified.

8.5 Geriatric Use

Clinical studies of MAYZENT did not include sufficient numbers of subjects aged 65 and over to determine whether they respond differently from younger subjects. Other reported clinical experience has not identified differences in responses between the elderly and younger patients. In general, dose selection for an elderly patient should be cautious, reflecting the greater frequency of decreased hepatic, renal, or cardiac function, and of concomitant disease or other drug therapy.

8.6 CYP2C9 Genotype

Before initiation of treatment with MAYZENT, test patients to determine CYP2C9 genotype.

MAYZENT is contraindicated in patients homozygous for CYP2C9*3 (i.e., CYP2C9*3/*3 genotype) because of substantially elevated siponimod plasma levels. The *3/*3 genotype is present in approximately 0.5% of white patients and 1% of Asian patients, and is less prevalent in other racial/ethnic groups.

MAYZENT dosage adjustment is recommended in patients with CYP2C9*1/*3 or *2/*3 genotype because of an increase in exposure to siponimod [see Dosage and Administration (2.3) and Clinical Pharmacology (12.5)]. The *1/*3 or *2/*3 genotypes are present in 2% to 20% of the population depending on ancestry.

There are other less frequently occurring polymorphisms in CYP2C9. Some polymorphisms, such as *5, *6, *8, and *11, are associated with decreased or loss of enzyme function. The impact of variants other than *2 and *3 on the pharmacokinetics of siponimod has not been evaluated. It is anticipated that variants that result in loss of CYP2C9 function (e.g., *6) will have similar effects on siponimod pharmacokinetics as the *3 variant [see Dosage and Administration (2.3) and Clinical Pharmacology (12.5)].

10 OVERDOSAGE

In patients with overdosage of MAYZENT, it is important to observe for signs and symptoms of bradycardia, which may include overnight monitoring. Regular measurements of pulse rate and blood pressure are required, and ECGs should be performed [see Warnings and Precautions (5.4, 5.8) and Clinical Pharmacology (12.2)].

There is no specific antidote to siponimod available. Neither dialysis nor plasma exchange would result in meaningful removal of siponimod from the body. The decrease in heart rate induced by MAYZENT can be reversed by atropine or isoprenaline.

11 DESCRIPTION

MAYZENT tablets contains siponimod, an S1P receptor modulator, as 2:1 co-crystal of siponimod and fumaric acid and has the following chemical name:

1-[[4-[(1E)-1-[[[4-Cyclohexyl-3-(trifluoromethyl)phenyl]methoxy]imino]ethyl]-2-ethylphenyl]methyl]-3-azetidinecarboxylic acid (2E)-2-butenedioate (2:1). Its molecular formula is C4H4O4•2C29H35F3N2O3, and its molecular weight is 1149.29 g/mol.

Its structure is shown below:

It is a white to almost white powder.

MAYZENT is provided as 0.25 mg, 1 mg, and 2 mg film-coated tablets for oral use. Each tablet contains 0.25 mg, 1 mg, or 2 mg siponimod, equivalent to 0.28 mg, 1.11 mg, or 2.22 mg as 2:1 co-crystal of siponimod and fumaric acid, respectively.

MAYZENT tablets contain the following inactive ingredients: colloidal silicon dioxide, crospovidone, glyceryl dibehenate, lactose monohydrate, microcrystalline cellulose, with a film coating containing iron oxides (black and red iron oxides for the 0.25 mg and 1 mg strengths and red and yellow iron oxides for the 2 mg strength), lecithin (soy), polyvinyl alcohol, talc, titanium dioxide, and xanthan gum.

12 CLINICAL PHARMACOLOGY

12.1 Mechanism of Action

Siponimod is an S1P receptor modulator. Siponimod binds with high affinity to S1P receptors 1 and 5. Siponimod blocks the capacity of lymphocytes to egress from lymph nodes, reducing the number of lymphocytes in peripheral blood. The mechanism by which siponimod exerts therapeutic effects in multiple sclerosis is unknown, but may involve reduction of lymphocyte migration into the central nervous system.

12.2 Pharmacodynamics

Immune System

MAYZENT induces a dose-dependent reduction of the peripheral blood lymphocyte count within 6 hours of the first dose, caused by the reversible sequestration of lymphocytes in lymphoid tissues.

With continued daily dosing, the lymphocyte count continues to decrease, reaching a nadir median (90% CI) lymphocyte count of approximately 0.560 (0.271 to 1.08) cells/nL in a typical CYP2C9*1/*1 or *1/*2, non-Japanese patient, corresponding to 20% to 30% of baseline. Low lymphocyte counts are maintained with chronic daily dosing [see Warnings and Precautions (5.1)].

Lymphocyte counts returned to the normal range in 90% of patients within 10 days of stopping therapy. After stopping MAYZENT treatment, residual lowering effects on peripheral lymphocyte count may persist for up to 3 to 4 weeks after the last dose [see Warnings and Precautions (5.1)].

Heart Rate and Rhythm

MAYZENT causes a transient reduction in heart rate and atrioventricular conduction upon treatment initiation [see Warnings and Precautions (5.4)]. The maximum decline in heart rate is seen in the first 6 hours post dose. Autonomic responses of the heart, including diurnal variation of heart rate and response to exercise, are not affected by siponimod treatment.

A transient, dose-dependent decrease in heart rate was observed during the initial dosing phase of MAYZENT, which plateaued at doses greater than or equal to 5 mg, and bradyarrhythmic events (AV blocks and sinus pauses) were detected at a higher incidence under MAYZENT treatment, compared to placebo.

No second-degree AV blocks of Mobitz type II or higher degree were observed. Most AV blocks and sinus pauses occurred above the recommended dose of 2 mg, with notably higher incidence under non-titrated conditions compared to dose titration conditions [see Dosage and Administration (2.2, 2.3)].

The decrease in heart rate induced by MAYZENT can be reversed by atropine or isoprenaline.

Beta-Blockers

The negative chronotropic effect of coadministration of siponimod and propranolol was evaluated in a dedicated pharmacodynamics (PD)/safety study. The addition of propranolol on top of siponimod at steady-state had less pronounced negative chronotropic effects (less than additive effect) than the addition of siponimod to propranolol at steady state (additive HR effect) [see Drug Interactions (7.3)].

Cardiac Electrophysiology

In a thorough QT study with doses of 2 mg (recommended dose) and 10 mg (five times the recommended dose) siponimod at steady-state, siponimod treatment resulted in a prolongation of QTc, with the maximum mean (upper bound of the two-sided 90% CI) of 7.8 (9.93) ms at 2 mg dose and 7.2 (9.72) ms at 10 mg dose. There was an absence of dose- and exposure-response relationship for QTc effects with the 5-fold dose and exposures achieved by the supratherapeutic dose. No subject had absolute QTcF greater than 480 ms or ΔQTcF greater than 60 ms for siponimod treatment.

Pulmonary Function

Dose-dependent reductions in absolute forced expiratory volume over 1 second were observed in MAYZENT-treated patients and were greater than in patients taking placebo [see Warnings and Precautions (5.5)].

12.3 Pharmacokinetics

Siponimod concentration increases in an apparent dose-proportional manner after multiple once-daily doses of siponimod 0.3 mg to 20 mg. Steady-state plasma concentrations are reached after approximately 6 days of once-daily dosing, and steady-state levels are approximately 2- to 3-fold greater than the initial dose. An up-titration regimen is used to reach the clinical therapeutic dose of siponimod of 2 mg after 6 days, and 4 additional days of dosing are required to reach the steady-state-plasma concentrations.

Absorption

The time (Tmax) to reach maximum plasma concentrations (Cmax) after oral administration of immediate release oral dosage forms of siponimod was about 4 hours (range, 3 to 8 hours). Siponimod absorption is extensive (greater than or equal to 70%, based on the amount of radioactivity excreted in urine and the amount of metabolites in feces extrapolated to infinity). The absolute oral bioavailability of siponimod is approximately 84%. After administration of siponimod 2 mg once daily over 10 days, a mean Cmax of 30.4 ng/mL and mean area under plasma concentration-time curve overdosing interval (AUCtau) of 558 h*ng/mL were observed on Day 10. Steady-state was reached after approximately 6 days of once-daily administration of siponimod.

Food Effect

Food intake resulted in delayed absorption (the median Tmax increased by approximately 2 to 3 hours). Food intake had no effect on the systemic exposure of siponimod (Cmax and AUC). Therefore, MAYZENT may be taken without regard to meals.

Distribution

Siponimod distributes to body tissues with a moderate mean volume of distribution of 124 L. Siponimod fraction found in plasma is 68% in humans. Animal studies show that siponimod readily crosses the blood-brain barrier. Protein binding of siponimod is greater than 99.9% in healthy subjects and in hepatic and renal impaired patients.

Elimination

Metabolism

Siponimod is extensively metabolized, mainly via CYP2C9 accounting for 80% of the metabolism in those who are normal metabolizers (i.e., those with the CYP2C9*1/*1 genotype). Residual elimination of siponimod is ascribed to various other cytochromes, including CYP3A4 (6%), which are considered to be minor across all CYP2C9 genotypes. The pharmacological activity of the main metabolites M3 and M17 is not expected to contribute to the clinical effect and the safety of siponimod in humans.

Excretion

An apparent systemic clearance (CL/F) of 3.11 L/h was estimated in MS patients. The apparent elimination half-life is approximately 30 hours.

Siponimod is eliminated from the systemic circulation mainly due to metabolism, and subsequent biliary/fecal excretion. Unchanged siponimod was not detected in urine.

Specific Populations

Male and Female Patients

Gender has no influence on siponimod pharmacokinetics (PK).

Racial or Ethnic Groups

The single-dose PK parameters were not different between Japanese and Caucasian healthy subjects, indicating absence of ethnic sensitivity on the PK of siponimod.

Patients with Renal Impairment

No dose adjustments are needed in patients with renal impairment. Mean siponimod half-life and Cmax (total and unbound) were comparable between subjects with severe renal impairment and healthy subjects. Unbound AUCs were only slightly increased (by 33%), compared to healthy subjects, and it is not expected to be clinically significant. The effects of end-stage renal disease or hemodialysis on the PK of siponimod has not been studied. Due to the high plasma protein binding (greater than 99.9%) of siponimod, hemodialysis is not expected to alter the total and unbound siponimod concentration and no dose adjustments are anticipated based on these considerations.

Patients with Hepatic Impairment

No dose adjustments for siponimod are needed in patients with hepatic impairment. The unbound siponimod AUC parameters are 15% and 50% higher in subjects with moderate and severe hepatic impairment, respectively, in comparison with healthy subjects for the 0.25 mg single dose studied. The increased unbound siponimod AUC in subjects with moderate and severe hepatic impairment is not expected to be clinically significant. The mean half-life of siponimod was unchanged in hepatic impairment.

Drug Interaction Studies

Siponimod (and Metabolites M3, M17) as a Causative Agent of Interaction

In vitro investigations indicated that siponimod and its major systemic metabolites M3 and M17 do not show any clinically relevant drug-drug interaction potential at the therapeutic dose of 2 mg once daily for all investigated CYP enzymes and transporters.

Clinical Studies and Model-Informed Approaches

Siponimod as an Object of Interaction

CYP2C9 is polymorphic and the CYP2C9 genotypes impact the metabolism of siponimod [see Drug Interactions (7.5)]. Residual elimination of siponimod is ascribed to various other cytochromes, with each responsible for a minor fraction of the elimination. Physiologically based PK modeling indicates that the inhibition and induction effects of CYP2C9, CYP3A4, or dual CYP2C9/CYP3A4 inhibitors or inducers on the systemic exposure of siponimod depend on the CYP2C9 genotype.

Coadministration of Siponimod with Strong CYP3A4 Inhibitors

The coadministration of clarithromycin (strong CYP3A4 inhibitor) 500 mg daily at steady-state and a single dose of siponimod 0.25 mg in CYP2C9*1/*3 healthy subjects led to a 1.09-fold increase in the AUC of siponimod, which is not clinically relevant.

Coadministration of Siponimod with Dual Moderate CYP2C9 and CYP3A4 Inhibitors

The coadministration of fluconazole (moderate CYP2C9/CYP3A4 dual inhibitor) 200 mg daily at steady-state and a single dose of siponimod 4 mg in CYP2C9*1/*1 healthy subjects led to a 2-fold increase in the AUC of siponimod and the mean siponimod terminal half-life was increased by 50%. The coadministration of fluconazole across all CYP2C9 genotypes (excluding CYP2C9*3/*3) is predicted to increase siponimod AUCtau,ss up to approximately 2.2-fold and Cmax,ss up to 1.9-fold in comparison to subjects with CYP2C9*1/*1 genotype without concomitant medications [see Drug Interactions (7.5)].

Coadministration of Siponimod with Dual Moderate CYP2C9 and Strong CYP3A4 Inducers

The coadministration of rifampin (dual moderate CYP2C9/strong CYP3A4 inducer) 600 mg daily and siponimod 2 mg daily in CY2C9*1/*1 subjects decreased siponimod AUCtau,ss and Cmax,ss by 57% and 45%, respectively. The coadministration of rifampin across all CYP2C9 genotypes (excluding CYP2C9*3/*3) is predicted to reduce siponimod AUCtau,ss by up to 70% in comparison to subjects with CYP2C9*1/*1 genotype without concomitant medications [see Drug Interactions (7.6)].

Coadministration of Siponimod with Moderate CYP3A4 Inducers

The coadministration of efavirenz (moderate CYP3A4 inducer) and siponimod across all CYP2C9 genotypes (excluding CYP2C9*3/*3) is predicted to reduce siponimod AUCtau,ss by approximately 35% for CYP2C9*1/*3 and 20% for CYP2C9*2/*3, in comparison with subjects with CYP2C9*1/*1 genotype without concomitant medications [see Drug Interactions (7.6)].

Oral Contraceptives

The effects of coadministration of a monophasic oral contraceptive (OC) containing 30 mcg ethinyl estradiol and 150 mcg levonorgestrel and siponimod 2 mg and 4 mg (twice the recommended dosage) once daily were assessed in 24 healthy female subjects (18 to 40 years of age; CYP2C9*1/*1 genotype). There were no clinically relevant effects on the PK or PD of the OC. No interaction studies have been performed with OCs containing other progestagens; however, an effect of siponimod on their exposure is not expected.

12.5 Pharmacogenomics

The CYP2C9 genotype has a significant impact on siponimod metabolism. After a single dose of 0.25 mg siponimod, AUCinf and AUClast were approximately 2- and 4-fold higher in subjects with the CYP2C9*2/*3 and CYP2C9*3/*3 genotypes, respectively, while there was only a minor increase of Cmax by 21% and 16%, respectively, compared to normal metabolizers (CYP2C9*1/*1). Mean half-life is prolonged in CYP2C9*2/*3 and CYP2C9*3/*3 carriers (51 hours and 126 hours, respectively).

An apparent systemic clearance (CL/F) of about 3.11 L/h was estimated in CYP2C9 normal metabolizer (CYP2C9*1/*1 and CYP2C9*1/*2) MS patients after multiple oral administrations of siponimod. Cl/F is 2.5, 1.9, 1.6, and 0.9 L/h in subjects with the CYP2C9*2/*2, CYP2C9*1/*3, CYP2C9*2/*3, and CYP2C9*3/*3 genotypes, respectively. The resultant increase in siponimod AUC was approximately 25%, 61%, 91%, and 285% higher in CYP2C9*2/*2, CYP2C9*1/*3, CYP2C9*2/*3, and CYP2C9*3/*3 subjects, respectively, as compared to CYP2C9*1/*1 subjects [see Dosage and Administration (2.1, 2.3) and Contraindications (4)]. As the apparent clearance estimated for CYP2C9*1/*2 subjects is comparable to that of CYP2C9*1/*1 subjects, similar siponimod exposure is expected for both genotypes.

Variants other than *2 and *3 may also lead to decreased or loss of CYP2C9 function (e.g., *5, *6, *8, *11) and may have substrate-specific effects. The frequency of certain CYP2C9 variants differs based on ancestry. The *2 and *3 variants are more prevalent in patients of European or Asian ancestry, while *5, *6, *8, and *11 are more prevalent in individuals of African ancestry [see Use in Specific Populations (8.6)].

13 NONCLINICAL TOXICOLOGY

13.1 Carcinogenesis, Mutagenesis, Impairment of Fertility

Carcinogenesis

Oral carcinogenicity studies of siponimod were conducted in mice and rats. In mice administered siponimod (0, 2, 8, or 25 mg/kg/day) for up to 104 weeks, there was an increase in malignant lymphoma in females at all doses and in hemangiosarcoma and combined hemangioma and hemangiosarcoma at all doses in males and females. The lowest dose tested is approximately 5 times the RHD of 2 mg/day, on a body surface area (mg/m^2) basis.

In rats, administration of siponimod (0, 10, 30, or 90 mg/kg/day in males; 0, 3, 10, or 30 mg/kg/day in females) for up to 104 weeks, there was an increase in thyroid follicular cell adenoma and combined thyroid follicular cell adenoma and carcinoma in males at the highest dose tested. These findings are considered secondary to liver enzyme induction in rats and are not considered relevant to humans. Plasma siponimod exposure (AUC) at the highest dose tested is approximately 200 times that in humans at the RHD.

Mutagenesis

Siponimod was negative in a battery of in vitro (Ames, chromosomal aberration in mammalian cells) and in vivo (micronucleus in mouse and rat) assays.

Impairment of Fertility

When siponimod was administered orally (0, 2, 20, or 200 mg/kg) to male rats (mated with untreated females) prior to and throughout the mating period, there was a dose-related increase in precoital interval at all doses. A decrease in implantation sites, an increase in preimplantation loss, and a decrease in the number of viable fetuses were observed at the highest dose tested. The higher no-effect dose for adverse effects on fertility (20 mg/kg) is approximately 100 times the RHD on a mg/m^2 basis.

When siponimod was administered orally (0, 0.1, 0.3, or 1 mg/kg) to female rats (mated with untreated males) prior to and during mating, and continuing to Day 6 of gestation, no effects on fertility were observed up to the highest dose tested (1 mg/kg). Plasma siponimod exposure (AUC) at the highest dose tested is approximately 16 times that in humans at the RHD.

14 CLINICAL STUDIES

The efficacy of MAYZENT was demonstrated in Study 1, a randomized, double-blind, parallel-group, placebo-controlled, time-to-event study in patients with secondary progressive multiple sclerosis (SPMS) who had evidence of disability progression in the prior 2 years, no evidence of relapse in 3 months prior to study enrollment, and an Expanded Disability Status Scale (EDSS) score of 3.0 to 6.5 at study entry (NCT 01665144).

Patients were randomized to receive either once daily MAYZENT 2 mg or placebo, beginning with a dose titration [see Dosage and Administration (2.2)]. Evaluations were performed at screening, every 3 months during the study, and at the time of a suspected relapse. MRI evaluations were performed at screening and every 12 months.

The primary endpoint of the study was the time to 3-month confirmed disability progression (CDP), defined as at least a 1-point increase from baseline in EDSS (0.5-point increase for patients with baseline EDSS of 5.5 or higher) sustained for 3 months. A prespecified hierarchical analysis consisted of the primary endpoint and 2 secondary endpoints, the time to 3-month confirmed worsening of at least 20% from baseline on the timed 25-foot walk test and the change from baseline in T2 lesion volume. Additional endpoints included annualized relapse rate (relapses/year) and MRI measures of inflammatory disease activity.

Study duration was variable for individual patients (median study duration was 21 months, range was 1 day to 37 months).

Study 1 randomized 1651 patients to either MAYZENT 2 mg (N = 1105) or placebo (N = 546); 82% of MAYZENT-treated patients and 78% of placebo-treated patients completed the study. Median age was 49.0 years, 95% of patients were white, and 60% female. The median disease duration was 16.0 years, and median EDSS score at baseline was 6.0 (56% of patients had ≥ 6.0 EDSS at baseline); 36% of patients had one or more relapses in the 2 years prior to study entry; 22% of those patients with available imaging had one or more gadolinium-enhancing lesions on their baseline MRI scan; 78% of patients had been previously treated with an MS therapy.

Results are presented in Table 4. MAYZENT was superior to placebo in reducing the risk of confirmed disability progression, based on a time-to-event analysis (hazard ratio 0.79, p < 0.0134; see Figure 1). MAYZENT did not significantly delay the time to 20% deterioration in the timed 25-foot walk, compared to placebo. Patients treated with MAYZENT had a 55% relative reduction in annualized relapse rate, compared to patients on placebo (nominal p-value < 0.0001). The absolute reduction in the annualized relapse rate was 0.089. Although MAYZENT had a significant effect on disability progression compared to placebo in patients with active SPMS (e.g., SPMS patients with an MS relapse in the 2 years prior to the study), the effect of MAYZENT in patients with non-active SPMS was not statistically significant (see Figure 2).

Table 4 Clinical and MRI Results From Study 1
 | MAYZENT | PLACEBO
Clinical outcomes
Proportion of patients with confirmed disability progressiona | 26% | 32%
Relative risk reduction | 21% (p = 0.0134)d
Absolute risk reduction | 6%
Proportion of patients with confirmed worsening in timed 25-foot walk | 40% | 41%
 | p = NS
Annualized relapse rateb | 0.071 | 0.160
Relative reduction (%) | 55% (p < 0.01)e
Absolute reduction | 0.089
 | p < 0.01e
MRI endpoints
Change from baseline in T2 lesion volume (mm^3) (95% CI)c | 184 (54; 314) | 879 (712; 1047)
 | p < 0.01e
Abbreviations: MRI, magnetic resonance imaging; NS, not statistically significant.
All analyses are based on the full analysis set (FAS), which includes all randomized subjects who took at least one dose of study medication.
p-values are two-sided.
aDefined as an increase of 1.0 point or more from the baseline Expanded Disability Status Scale (EDSS) score for patients with baseline score of 5.5
or less, or 0.5 or more when the baseline score is greater than 5.5. Progression confirmed at 3 months. Cox proportional hazard model.
bDefined as the average number of confirmed relapses per year (estimated from negative binomial regression model for recurrent events).
cAdjusted mean averaged over Months 12 and 24.
dStatistically significant.
eNominal p value, not corrected for multiple comparisons.

Figure 1 Time to Confirmed Disability Progression Based on EDSS (Study 1)

Figure 2 Time to Confirmed Disability Progression Based on EDSS (Study 1), Subgroup Analysis

*HR and 95% CI presented are model-based estimates for a range of values of age and Expanded Disability Status Scale (EDSS).

16 HOW SUPPLIED/STORAGE AND HANDLING

16.1 How Supplied

MAYZENT film-coated tablets are supplied as follows:

0.25 mg tablet: Pale red, unscored, round biconvex film-coated tablet with beveled edges, debossed with on one side and ‘T’ on other side.

Starter Pack for 1-mg maintenance dosage – blister card of seven 0.25 mg tablets in a calendarized blister wallet...............NDC 0078-0979-89

Starter Pack for 2-mg maintenance dosage – blister card of twelve 0.25 mg tablets in a calendarized blister wallet...............NDC 0078-0979-12

Bottle of 28 tablets........................................................................................................................NDC 0078-0979-50

1 mg tablet: Violet white, unscored, round biconvex film-coated tablet with beveled edges, debossed with on one side and ‘L’ on other side.

Bottle of 30 tablets.........................................................................................................................NDC 0078-1014-15

2 mg tablet: Pale yellow, unscored, round biconvex film-coated tablet with beveled edges, debossed with on one side and ‘II’ on other side.

Bottle of 30 tablets.........................................................................................................................NDC 0078-0986-15

Bottle of 15 tablets.........................................................................................................................NDC 0078-0986-45

16.2 Storage and Handling

Unopened Containers

Store MAYZENT 0.25 mg, 1 mg, and 2 mg film-coated tablets in a refrigerator between 2°C to 8°C (36°F to 46°F). After dispensed by pharmacy to patient, MAYZENT 0.25 mg, 1 mg, and 2 mg film-coated tablets may be stored at 20°C to 25°C (68°F to 77°F) [see USP Controlled Room Temperature] for up to 3 months.

Opened Containers

Bottles

MAYZENT 0.25 mg, 1 mg, and 2 mg film-coated tablets may be stored at 20°C to 25°C (68°F to 77°F) [see USP Controlled Room Temperature] for up to 3 months. Do not refrigerate after opening.

Starter Pack/Blister Card

MAYZENT 0.25 mg film-coated tablets may be stored at 20°C to 25°C (68°F to 77°F) [see USP Controlled Room Temperature] for up to 3 months. Do not refrigerate after opening. Store in original calendarized blister wallet container.

17 PATIENT COUNSELING INFORMATION

Advise the patient to read the FDA-approved patient labeling (Medication Guide).

Administration

Tell patients not to discontinue MAYZENT without first discussing this with the prescribing physician. Advise patients to contact their physician if they accidently take more MAYZENT than prescribed.

Instruct patients to administer tablets whole; do not split, crush, or chew MAYZENT tablets.

Risk of Infections

Inform patients that they may have an increased risk of infections, some of which could be life-threatening, when taking MAYZENT, and that they should contact their physician if they develop symptoms of infection [see Warnings and Precautions (5.1)]. Advise patients that the use of some vaccines containing live virus (live-attenuated vaccines) should be avoided during treatment with MAYZENT and MAYZENT should be paused 1 week prior and until 4 weeks after a planned vaccination. Recommend that patients postpone treatment with MAYZENT for at least 1 month after VZV vaccination. Inform patients that prior or concomitant use of drugs that suppress the immune system may increase the risk of infection.

Progressive Multifocal Leukoencephalopathy

Inform patients that cases of progressive multifocal leukoencephalopathy (PML) have occurred in patients who received MAYZENT. Inform the patient that PML is characterized by a progression of deficits and usually leads to death or severe disability over weeks or months. Instruct the patient of the importance of contacting their doctor if they develop any symptoms suggestive of PML. Inform the patient that typical symptoms associated with PML are diverse, progress over days to weeks, and include progressive weakness on one side of the body or clumsiness of limbs, disturbance of vision, and changes in thinking, memory, and orientation leading to confusion and personality changes [see Warnings and Precautions (5.2)].

Macular Edema

Advise patients that MAYZENT may cause macular edema, and that they should obtain an eye exam near the start of treatment with MAYZENT, have their eyes monitored periodically by an eye care professional while receiving therapy, and contact their healthcare provider if they experience any changes in their vision while taking MAYZENT [see Warnings and Precautions (5.3)]. Inform patients with diabetes mellitus or a history of uveitis that their risk of macular edema is increased.

Cardiac Effects

Advise patients that initiation of MAYZENT treatment results in transient decrease in heart rate [see Warnings and Precautions (5.4)]. Inform patients that to reduce this effect, dosage titration is required. Advise patients that dosage titration is also required if a dose is missed for more than 24 hours during the titration or if 4 or more consecutive daily maintenance doses are missed [see Dosage and Administration (2.2, 2.3, 2.5) and Warnings and Precautions (5.4)]. Inform certain patients with certain preexisting cardiac conditions that they will need to be observed in the doctor's office or other facility for at least 6 hours after the first dose and after reinitiation if treatment is interrupted or discontinued for certain periods [see Dosage and Administration (2.4)].

Respiratory Effects

Advise patients that they should contact their physician if they experience new onset or worsening of dyspnea [see Warnings and Precautions (5.5)].

Liver Injury

Inform patients that MAYZENT may increase liver enzymes. Advise patients that they should contact their physician if they experience any unexplained nausea, vomiting, abdominal pain, fatigue, anorexia, or jaundice and/or dark urine during treatment [see Warnings and Precautions (5.6)].

Cutaneous Malignancies

Inform patients that the risk of BCC and SCC is increased with the use of MAYZENT and that cases of melanoma have been reported. Advise patients that any suspicious skin lesions should be promptly evaluated. Advise patients to limit exposure to sunlight and ultraviolet light by wearing protective clothing and using a sunscreen with a high protection factor [see Warnings and Precautions (5.7)].

Pregnancy and Fetal Risk

Inform patients that, based on animal studies, MAYZENT may cause fetal harm [see Warnings and Precautions (5.9)]. Discuss with women of childbearing age whether they are pregnant, might be pregnant, or are trying to become pregnant. Advise women of childbearing potential of the need for effective contraception during treatment with MAYZENT and for 10 days after stopping MAYZENT. Advise a female patient to immediately inform her prescriber if she is pregnant or planning to become pregnant [see Warnings and Precautions (5.9) and Use in Specific Populations (8.1, 8.3)].

Pregnancy Exposure Registry

Instruct patients that if they are pregnant or plan to become pregnant while taking MAYZENT, they should inform their healthcare provider. Encourage patients to enroll in the MotherToBaby Pregnancy Study in Multiple Sclerosis if they become pregnant while taking MAYZENT [see Use in Specific Populations (8.1)].

Posterior Reversible Encephalopathy Syndrome

Advise patients to immediately report to their healthcare provider any symptoms involving sudden onset of severe headache, altered mental status, visual disturbances, or seizure. Inform patients that delayed treatment could lead to permanent neurological sequelae [see Warnings and Precautions (5.10)].

Severe Increase in Disability After Stopping MAYZENT

Inform patients that severe increase in disability has been reported after discontinuation of another S1P receptor modulator like MAYZENT. Advise patients to contact their physician if they develop worsening symptoms of MS following discontinuation of MAYZENT [see Warnings and Precautions (5.12)].

Immune System Effects After Stopping MAYZENT

Advise patients that MAYZENT continues to have effects, such as lowering effects on peripheral lymphocyte count, for up to 3 to 4 weeks after the last dose [see Warnings and Precautions (5.13)].

Storage and Handling

Inform patients that MAYZENT may be stored at room temperature for up to 3 months. If patients need to store MAYZENT for more than 3 months, containers should remain unopened and stored in a refrigerator until use [see How Supplied/Storage and Handling (16.2)].

Distributed by:
Novartis Pharmaceuticals Corporation
East Hanover, New Jersey 07936

MAYZENT is a registered trademark of Novartis AG

© Novartis

T2025-51

MEDICATION GUIDE
MAYZENT (Māʹzĕnt)
(siponimod)
tablets, for oral use

What is the most important information I should know about MAYZENT?
1. MAYZENT may cause serious side effects, including: Slow heart rate (bradycardia or bradyarrhythmia) when you start taking MAYZENT. MAYZENT can cause your heart rate to slow down, especially after you take your first dose. You should have a test, called an electrocardiogram (ECG), to check the electrical activity of your heart, before you take your first dose of MAYZENT.
During the initial updosing period (4 days for the 1 mg daily dose or 5 days for the 2 mg daily dose), if you miss 1 or more doses of MAYZENT, you need to restart the updosing. Call your healthcare provider if you miss a dose of MAYZENT. See “How should I take MAYZENT?”
2. Infections. MAYZENT can increase your risk of serious infections that can be life-threatening and cause death. MAYZENT lowers the number of white blood cells (lymphocytes) in your blood. This will usually go back to normal within 3 to 4 weeks of stopping treatment. Your healthcare provider should review a recent blood test of your white blood cells before you start taking MAYZENT.
Call your healthcare provider right away if you have any of these symptoms of an infection during treatment with MAYZENT and for 3 to 4 weeks after your last dose of MAYZENT:

- fever
- tiredness
- body aches
- chills
- nausea

- vomiting
- headache with fever, neck stiffness, sensitivity to light, nausea, confusion (these may be symptoms of meningitis, an infection of the lining around your brain and spine and/or encephalitis, an infection of the brain)

3. Progressive multifocal leukoencephalopathy (PML). MAYZENT can increase your risk for PML, which is a rare brain infection that usually leads to death or severe disability. If PML happens, it usually happens in people with weakened immune systems but has happened in people who do not have weakened immune systems. Symptoms of PML get worse over days to weeks. Call your doctor right away if you have any new or worsening neurologic symptoms that have lasted several days, including:

- weakness on 1 side of your body
- loss of coordination in your arms and legs
- decreased strength
- problems with balance

- changes in your vision
- changes in your thinking or memory
- confusion
- changes in your personality

4. A problem with your vision called macular edema. Macular edema can cause some of the same vision symptoms as a multiple sclerosis (MS) attack (optic neuritis). You may not notice any symptoms with macular edema. If macular edema happens, it usually starts in the first 1 to 4 months after you start taking MAYZENT but can happen at any time. Your healthcare provider should test your vision around the time you start taking MAYZENT, periodically while taking MAYZENT, and any time you notice vision changes during treatment with MAYZENT. Your risk of macular edema is higher if you have diabetes or have had an inflammation of your eye called uveitis.
Call your healthcare provider right away if you have any of the following symptoms:

- blurriness or shadows in the center of your vision
- a blind spot in the center of your vision

- sensitivity to light
- unusually colored (tinted) vision

See "What are the possible side effects of MAYZENT?" for more information about side effects.

What is MAYZENT?
MAYZENT is a prescription medicine that is used to treat relapsing forms of multiple sclerosis, to include clinically isolated syndrome, relapsing-remitting disease, and active secondary progressive disease, in adults.
It is not known if MAYZENT is safe and effective in children.

Who should not take MAYZENT?
Do not take MAYZENT if you:

- have a CYP2C9*3/*3 genotype. Before starting treatment with MAYZENT, your CYP2C9 genotype should be determined by your healthcare provider. Ask your healthcare provider if you are not sure.
- have had a heart attack, chest pain called unstable angina, stroke or mini stroke (transient ischemic attack or TIA), or certain types of heart failure in the last 6 months
- have certain types of heart block or irregular or abnormal heartbeat (arrhythmia), unless you have a pacemaker

What should I tell my healthcare provider before taking MAYZENT?
Before taking MAYZENT, tell your healthcare provider about all of your medical conditions, including if you:

- have an irregular or abnormal heartbeat
- have a history of stroke or other diseases related to blood vessels in the brain
- have breathing problems, including during your sleep
- have a fever or infection, or you are unable to fight infections due to a disease or taking medicines that lower your immune system. Tell your healthcare provider if you have had chickenpox or have received the vaccine for chickenpox. Your healthcare provider may do a blood test for chickenpox virus. You may need to get the full course of vaccine for chickenpox and then wait 1 month before you start taking MAYZENT.
- have slow heart rate
- have liver problems
- have diabetes
- have eye problems, especially an inflammation of the eye called uveitis
- had or now have any types of skin cancer, including basal cell carcinoma (BCC), melanoma, or squamous cell carcinoma (SCC)
- have high blood pressure
- are pregnant or plan to become pregnant. MAYZENT may harm your unborn baby. Talk to your healthcare provider right away if you become pregnant while taking MAYZENT or if you become pregnant within 10 days after you stop taking MAYZENT.
  - If you are a woman who can become pregnant, you should use effective birth control during your treatment with MAYZENT and for at least 10 days after you stop taking MAYZENT.
  - Pregnancy Registry: There is a registry for women who become pregnant during treatment with MAYZENT. If you become pregnant while taking MAYZENT, talk to your healthcare provider about registering with the MotherToBaby Pregnancy Study in Multiple Sclerosis. The purpose of this registry is to collect information about your health and your baby’s health.
    For more information or to register, contact MotherToBaby by calling 1-877-311-8972, by sending an email to MotherToBaby@health.ucsd.edu, or go to www.mothertobaby.org/join-study.
- are breastfeeding or plan to breastfeed. It is not known if MAYZENT passes into your breast milk. Talk to your healthcare provider about the best way to feed your baby if you take MAYZENT.

Tell your healthcare provider about all the medicines you take, including prescription medicines, over-the-counter medicines, vitamins, and herbal supplements. Especially tell your healthcare provider if you:

- take medicines to control your heart rhythm (antiarrhythmics), or blood pressure (antihypertensives), or heartbeat (such as calcium channel blockers or beta-blockers)
- take medicines that affect your immune system, such as beta-interferon or glatiramer acetate, or any of these medicines that you took in the past
- have recently received a live vaccine. You should avoid receiving live vaccines during treatment with MAYZENT. MAYZENT should be stopped 1 week before and for 4 weeks after receiving a live vaccine. If you receive a live vaccine, you may get the infection that the vaccine was meant to prevent. Vaccines may not work as well when given during treatment with MAYZENT.

Know the medicines you take. Keep a list of your medicines with you to show your healthcare provider and pharmacist when you get a new medicine.

Using MAYZENT and other medicines together may affect each other causing serious side effects.

How should I take MAYZENT?
The daily maintenance dose of MAYZENT is either 1 mg or 2 mg, depending on your CYP2C9 genotype. Ask your healthcare provider if you are not sure about your daily maintenance dose.
Do not split, crush, or chew MAYZENT tablets; take tablets whole.
Start your treatment with MAYZENT using the following titration schedule with your starter pack:

For the 1 mg daily maintenance dose, use a 7-tablet starter pack:
Day 1
Day 2
Day 3
Day 4
Day 5 and every day after

Tablets a day
1 x 0.25 mg tablet
1 x 0.25 mg tablet
2 x 0.25 mg tablet
3 x 0.25 mg tablet
1 x 1 mg tablet

For the 2 mg daily maintenance dose, use a 12-tablet starter pack:
Day 1
Day 2
Day 3
Day 4
Day 5
Day 6 and every day after

Tablets a day
1 x 0.25 mg tablet
1 x 0.25 mg tablet
2 x 0.25 mg tablet
3 x 0.25 mg tablet
5 x 0.25 mg tablet
1 x 2 mg tablet

- Take MAYZENT exactly as your healthcare provider tells you. Do not change your dose or stop taking MAYZENT unless your healthcare provider tells you to.
- Take MAYZENT 1 time each day.
- Take MAYZENT with or without food.
- If you miss 1 or more doses of MAYZENT during the initial dose titration, you need to restart the medication.
- If you miss a dose of MAYZENT after the initial dose-titration, take it as soon as you remember.
- If MAYZENT treatment is stopped for 4 days in a row, treatment has to be restarted with the titration.
- Do not stop taking MAYZENT without talking with your healthcare provider first.

What are the possible side effects of MAYZENT?
MAYZENT may cause serious side effects, including:

- See "What is the most important information I should know about MAYZENT?"
- increased blood pressure. Your healthcare provider should check your blood pressure during treatment with MAYZENT.
- liver problems. MAYZENT may cause liver problems. Your healthcare provider should do blood tests to check your liver before you start taking MAYZENT. Call your healthcare provider right away if you have any of the following symptoms of liver problems:

◦ nausea
◦ vomiting
◦ stomach pain
◦ tiredness

◦ loss of appetite
◦ your skin or the whites of your eyes turn yellow
◦ dark urine

- breathing problems. Some people who take MAYZENT have shortness of breath. Call your healthcare provider right away if you have new or worsening breathing problems.
- swelling and narrowing of the blood vessels in your brain. A condition called PRES (Posterior Reversible Encephalopathy Syndrome) has happened with drugs in the same class. Symptoms of PRES usually get better when you stop taking MAYZENT. However, if left untreated, it may lead to a stroke. Call your healthcare provider right away if you have any of the following symptoms:

◦ sudden severe headache
◦ sudden confusion

◦ sudden loss of vision or other changes in your vision
◦ seizure

- severe worsening of multiple sclerosis after stopping MAYZENT. When MAYZENT is stopped, symptoms of MS may return and become worse compared to before or during treatment. Always talk to your doctor before you stop taking MAYZENT for any reason. Tell your healthcare provider if you have worsening symptoms of MS after stopping MAYZENT.
- types of skin cancer, including basal cell carcinoma, melanoma, and squamous cell carcinoma. Tell your doctor if you have any changes in the appearance of your skin, including changes in a mole, a new darkened area on your skin, a sore that does not heal, or growths on your skin, such as a bump that may be shiny, pearly white, skin-colored, or pink. Your doctor should check your skin for any changes at the start of and during treatment with MAYZENT. Limit the amount of time you spend in sunlight and ultraviolet (UV) light. Wear protective clothing and use a sunscreen with a high sun protection factor.

The most common side effects of MAYZENT include:

- headache
- high blood pressure (hypertension)
- abnormal liver tests

Tell your healthcare provider if you have any side effects that bother you or that do not go away.

These are not all of the possible side effects of MAYZENT. For more information, ask your healthcare provider or pharmacist. Call your doctor for medical advice about side effects. You may report side effects to FDA at 1-800-FDA-1088.

How should I store MAYZENT?
Unopened Containers
MAYZENT 0.25 mg, 1 mg, and 2 mg tablets may be stored at room temperature between 68°F to 77°F (20°C to 25°C) for up to 3 months. If you need to store MAYZENT tablets for more than 3 months, containers should remain unopened and stored in a refrigerator between 36°F to 46°F (2°C to 8°C) until use.
Opened Containers
Bottles
MAYZENT 0.25 mg, 1 mg, and 2 mg tablets may be stored at room temperature between 68°F to 77°F (20°C to 25°C) for up to 3 months. Do not refrigerate after opening.
Starter Pack/Blister Card
MAYZENT 0.25 mg tablets may be stored at room temperature between 68°F to 77°F (20°C to 25°C) for up to 3 months. Do not refrigerate after opening. Store in original calendarized blister wallet container.
Keep MAYZENT and all medicines out of the reach of children.

General information about the safe and effective use of MAYZENT.
Medicines are sometimes prescribed for purposes other than those listed in a Medication Guide. Do not use MAYZENT for a condition for which it was not prescribed. Do not give MAYZENT to other people, even if they have the same symptoms you have. It may harm them. You can ask your pharmacist or healthcare provider for more information about MAYZENT that is written for health professionals.

What are the ingredients in MAYZENT?

Active ingredient: siponimod

Inactive ingredients: colloidal silicon dioxide, crospovidone, glyceryl dibehenate, lactose monohydrate, microcrystalline cellulose, with a film coating containing iron oxides (black and red iron oxides for the 0.25 mg and 1 mg strengths and red and yellow iron oxides for the 2 mg strength), lecithin (soy), polyvinyl alcohol, talc, titanium dioxide, and xanthan gum.

Distributed by: Novartis Pharmaceuticals Corporation, East Hanover, New Jersey 07936

For more information, go to www.mayzent.com or call 1-888-669-6682.

This Medication Guide has been approved by the U.S. Food and Drug Administration

Revised: August 2025

T2025-52

PRINCIPAL DISPLAY PANEL

NDC 0078-0979-50

Rx only

MAYZENT®

(siponimod) tablets

0.25 mg*

28 tablets

Dispense with accompanying Medication Guide.

NOVARTIS

PRINCIPAL DISPLAY PANEL

NDC 0078-1014-15

Rx only

MAYZENT®

(siponimod) tablets

1 mg*

30 tablets

Dispense with accompanying Medication Guide.

Swallow tablets whole. DO NOT split tablets.

NOVARTIS

PRINCIPAL DISPLAY PANEL

NDC 0078-0986-15

Rx only

MAYZENT®

(siponimod) tablets

2 mg*

30 tablets

Dispense with accompanying Medication Guide.

Swallow tablets whole. DO NOT split tablets.

NOVARTIS